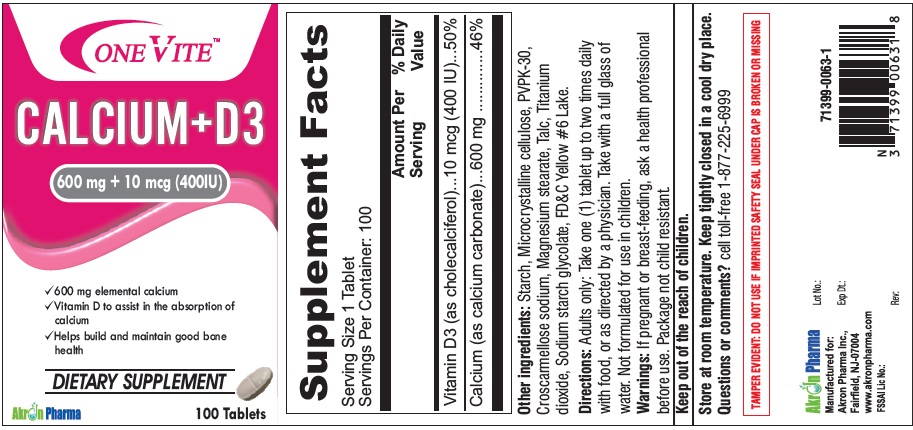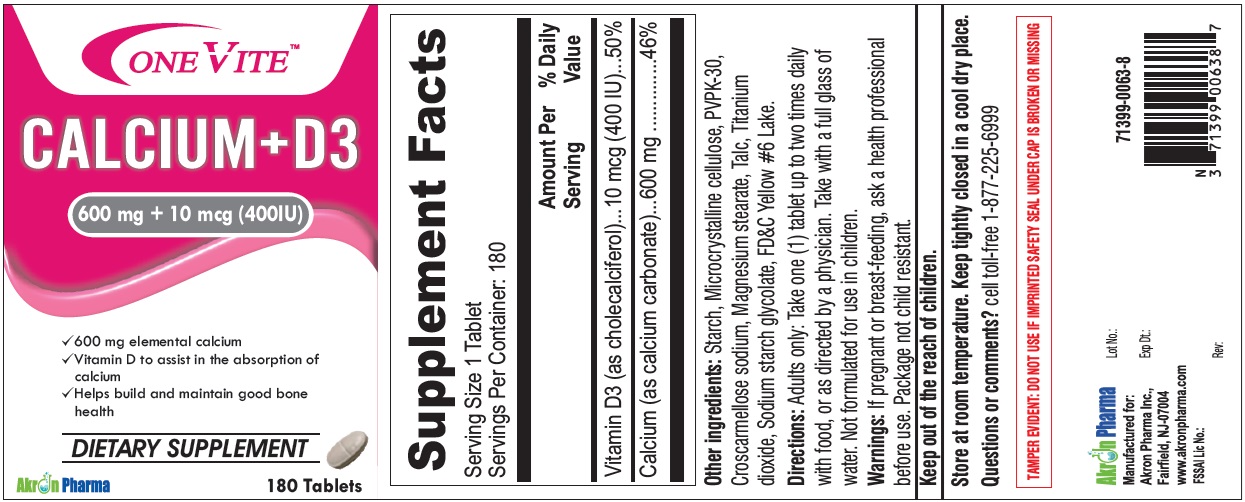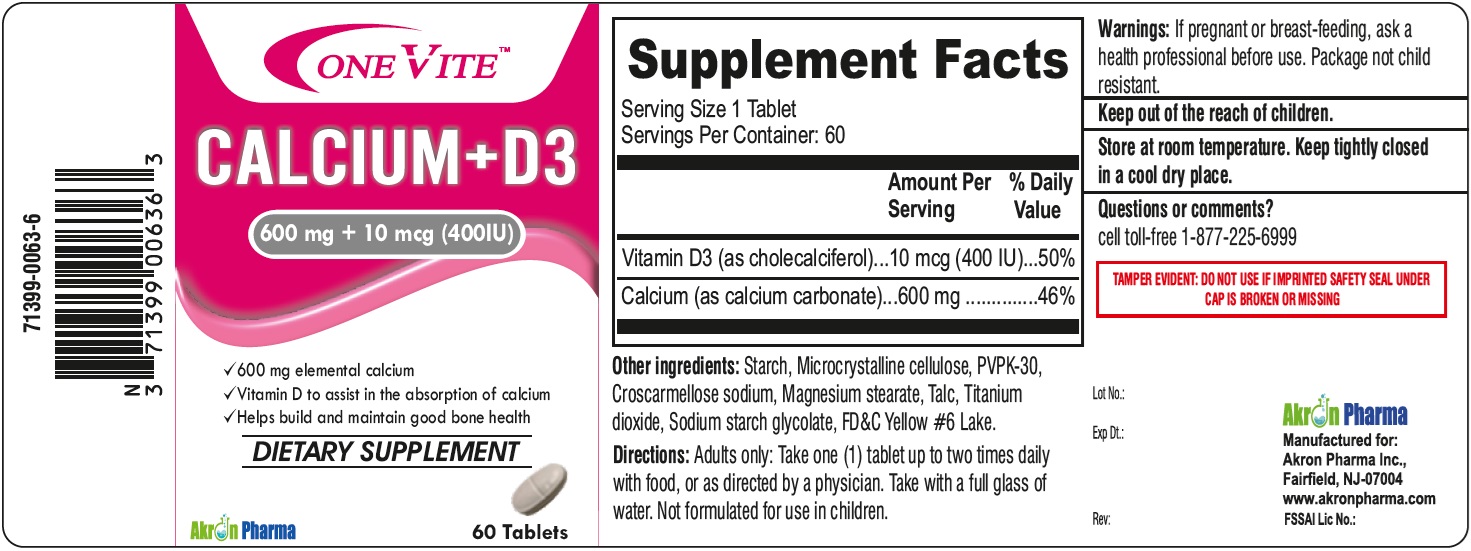 DRUG LABEL: ONEVITE
NDC: 71399-0063 | Form: TABLET
Manufacturer: Akron Pharma Inc.
Category: other | Type: DIETARY SUPPLEMENT
Date: 20240509

ACTIVE INGREDIENTS: CHOLECALCIFEROL 10 ug/1 1; CALCIUM CARBONATE 600 mg/1 1

ONEVITE
CALCIUM+D3
600 mg + 10mcg (400 IU)

Dietary Supplement Facts

Serving Size 1 Tablet
Servings Per Container: 60

 | Amount Per Serving | % Daily Value
Vitamin D3 (as cholecalciferol) | 10 mcg (400 IU) | 50%
Calcium (as calcium carbonate) | 600 mg | 46%

Other ingredients: Starch, Microcrystalline cellulose, PVPK-30, Croscarmellose sodium, Magnesium stearate, Talc, Titanium dioxide, Sodium starch glycolate, FD&C Yellow #6 Lake.

Directions

Adults only: Take one (1) tablet up to two times daily with food, or as directed by a physician. Take with a full glass of water. Not formulated for use in children.

Warnings: If pregnant or breast-feeding, ask a health professional before use. Package not child resistant.
Keep out of the reach of children.

Store at room temperature. Keep tightly closed in a cool dry place.

TAMPER EVIDENT: DO NOT USE IF IMPRINTED SAFETY SEAL UNDER CAP IS BROKEN OR MISSING

Questions or comments?
call toll-free 1-877-225-6999

Manufactured for:

Akron Pharma Inc.,

Fairfield, NJ-07004

www.akronpharma.com

PACKAGE LABEL

60 Tablets:

100 Tablets:

180 Tablets: